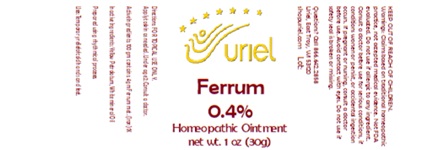 DRUG LABEL: Ferrum 0.4
NDC: 48951-4196 | Form: OINTMENT
Manufacturer: Uriel Pharmacy, Inc
Category: homeopathic | Type: HUMAN OTC DRUG LABEL
Date: 20250207

ACTIVE INGREDIENTS: IRON 1 [hp_X]/1 g
INACTIVE INGREDIENTS: PETROLATUM; MINERAL OIL

Ferrum 0.4

INDICATIONS AND USAGE

Directions: FOR TOPICAL USE ONLY.

DOSAGE AND ADMINISTRATION

Directions: FOR TOPICAL USE ONLY.

ACTIVE INGREDIENT

Active Ingredients: 100 gm contains: 4 gm Ferrum met. (Iron) 1X

Inactive Ingredients: Yellow Petrolatum, White mineral Oil

Prepared using rhythmical processes.

PURPOSE

Uses: Temporary relief of cold hands and feet.

KEEP OUT OF REACH OF CHILDREN

Uses: Temporary relief of cold hands and feet.

WARNINGS

Warnings: Claims based on traditional homeopathic practice, not accepted medical evidence. Not FDA evaluated. Do not use if allergic to any ingredient. Consult a doctor before use for serious conditions, if conditions worsen or persist, or accidental ingestion occurs. If pregnant or nursing, consult a doctor before use. Avoid contact with eyes. Do not use if safety seal is broken or missing.

Questions? Call 866.642.2858
Uriel, East Troy, WI 53120
shopuriel.com Lot: